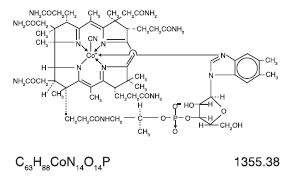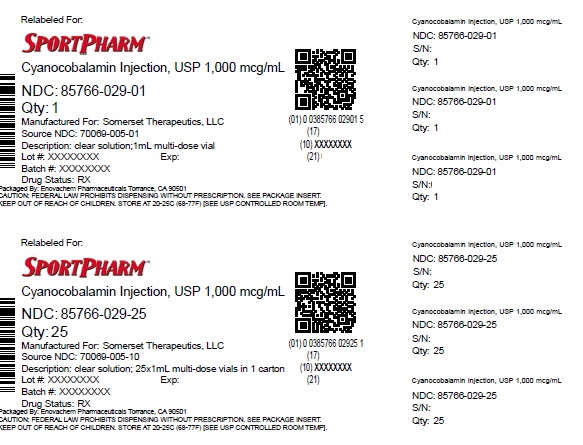 DRUG LABEL: cyanocobalamin
NDC: 85766-029 | Form: INJECTION
Manufacturer: Sportpharm LLC
Category: prescription | Type: HUMAN PRESCRIPTION DRUG LABEL
Date: 20260205

ACTIVE INGREDIENTS: CYANOCOBALAMIN 1000 ug/1 mL
INACTIVE INGREDIENTS: BENZYL ALCOHOL 15 mg/1 mL; SODIUM CHLORIDE 9 mg/1 mL; HYDROCHLORIC ACID; SODIUM HYDROXIDE; WATER

Cyanocobalamin Injection USP 1000 mcg/mL

DESCRIPTION

Cyanocobalamin Injection, USP is a sterile solution of cyanocobalamin for intramuscular or subcutaneous use.

Each mL contains 1,000 mcg cyanocobalamin; sodium chloride 0.9%; benzyl alcohol 1.5%; Water for Injection q.s.; Hydrochloric acid and/or sodium hydroxide for pH adjustment if necessary (4.5-7.0).

Cyanocobalamin appears as dark, red crystals or as an amorphous or crystalline, red powder. It is very hygroscopic in the anhydrous form, and sparingly soluble in water (1:80). It is stable to autoclaving for short periods at 121°C. The Vitamin B12coenzymes are very unstable in light.

The chemical name is 5,6-dimethyl-benzimidazolyl cyanocobamide. The cobalt content is 4.34%. The structural formula is represented below:

CLINICAL PHARMACOLOGY

Vitamin B12is essential to growth, cell reproduction, hematopoiesis, nucleoprotein and myelin synthesis.

Cyanocobalamin is quantitatively and rapidly absorbed from intramuscular and subcutaneous sites of injection; the plasma level of the compound reaches its peak within one hour after intramuscular injection. Absorbed Vitamin B12is transported via specific B12binding proteins, transcobalamin I and II to the various tissues. The liver is the main organ for Vitamin B12storage.

Within 48 hours after injection of 100 or 1,000 mcg of Vitamin B12, 50 to 98% of the injected dose may appear in the urine. The major portion is excreted within the first eight hours. Intravenous administration results in even more rapid excretion with little opportunity for liver storage.

Gastrointestinal absorption of Vitamin B12depends on the presence of sufficient intrinsic factor and calcium ions. Intrinsic factor deficiency causes pernicious anemia, which may be associated with subacute combined degeneration of the spinal cord. Prompt parenteral administration of Vitamin B12prevents progression of neurologic damage.

The average diet supplies about 5 to 15 mcg/day of Vitamin B12in a protein-bound form that is available for absorption after normal digestion. Vitamin B12is not present in foods of plant origin, but is abundant in foods of animal origin. In people with normal absorption, deficiencies have been reported only in strict vegetarians who consume no products of animal origin (including no milk products or eggs).

Vitamin B12is bound to intrinsic factor during transit through the stomach; separation occurs in the terminal ileum in the presence of calcium, and Vitamin B12enters the mucosal cell for absorption. It is then transported by the transcobalamin binding proteins. A small amount (approximately 1% of the total amount ingested) is absorbed by simple diffusion, but this mechanism is adequate only with very large doses. Oral absorption is considered too undependable to rely on in patients with pernicious anemia or other conditions resulting in malabsorption of Vitamin B12.

Cyanocobalamin is the most widely used form of Vitamin B12, and has hematopoietic activity apparently identical to that of the antianemia factor in purified liver extract. Hydroxocobalamin is equally as effective as cyanocobalamin, and they share the cobalamin molecular structure.

INDICATIONS AND USAGE

Cyanocobalamin is indicated for Vitamin B12deficiencies due to malabsorption which may be associated with the following conditions:

Addisonian (pernicious) anemia

Gastrointestinal pathology, dysfunction, or surgery, including gluten enteropathy or sprue, small bowel bacterial overgrowth, total or partial gastrectomy

Fish tapeworm infestation

Malignancy of pancreas or bowel

Folic acid deficiency

It may be possible to treat the underlying disease by surgical correction of anatomic lesions leading to small bowel bacterial overgrowth, expulsion of fish tapeworm, discontinuation of drugs leading to vitamin malabsorption (see Drug/Laboratory Test Interactions), use of a gluten-free diet in nontropical sprue, or administration of antibiotics in tropical sprue. Such measures remove the need for long-term administration of cyanocobalamin.

Requirements of Vitamin B12in excess of normal (due to pregnancy, thyrotoxicosis, hemolytic anemia, hemorrhage, malignancy, hepatic and renal disease) can usually be met with oral supplementation.

Cyanocobalamin injection is also suitable for the Vitamin B12absorption test (Schilling test).

CONTRAINDICATIONS

Sensitivity to cobalt and/or Vitamin B12is a contraindication.

WARNINGS

This product contains aluminum that may be toxic. Aluminum may reach toxic levels with prolonged parenteral administration if kidney function is impaired. Premature neonates are particularly at risk because their kidneys are immature, and they require large amounts of calcium and phosphate solutions, which contain aluminum.

Research indicates that patients with impaired kidney function, including premature neonates, who receive parenteral levels of aluminum at greater than 4 to 5 mcg/kg/day accumulate aluminum at levels associated with central nervous system and bone toxicity. Tissue loading may occur at even lower rates of administration.

Patients with early Leber's disease (hereditary optic nerve atrophy) who were treated with cyanocobalamin suffered severe and swift optic atrophy.

Hypokalemia and sudden death may occur in severe megaloblastic anemia which is treated intensely.

Anaphylactic shock and death have been reported after parenteral Vitamin B12administration. An intradermal test dose is recommended before cyanocobalamin injection is administered to patients suspected of being sensitive to this drug.

This product contains benzyl alcohol. Benzyl alcohol has been reported to be associated with a fatal ''Gasping Syndrome'' in premature infants.

PRECAUTIONS

General

Vitamin B12deficiency that is allowed to progress for longer than three months may produce permanent degenerative lesions of the spinal cord. Doses of folic acid greater than 0.1 mg/day may result in hematologic remission in patients with Vitamin B12deficiency. Neurologic manifestations will not be prevented with folic acid, and if not treated with Vitamin B12, irreversible damage will result.

Doses of cyanocobalamin exceeding 10 mcg daily may produce hematologic response in patients with folate deficiency. Indiscriminate administration may mask the true diagnosis.

Information for Patients

Patients with pernicious anemia should be instructed that they will require monthly injections of Vitamin B12for the remainder of their lives. Failure to do so will result in return of the anemia and in development of incapacitating and irreversible damage to the nerves of the spinal cord. Also, patients should be warned about the danger of taking folic acid in place of Vitamin B12, because the former may prevent anemia but allow progression of subacute combined degeneration.

A vegetarian diet which contains no animal products (including milk products or eggs) does not supply any Vitamin B12. Patients following such a diet should be advised to take oral Vitamin B12regularly. The need for Vitamin B12is increased by pregnancy and lactation. Deficiency has been recognized in infants of vegetarian mothers who were breast fed, even though the mothers had no symptoms of deficiency at the time.

Contains no more than 57 mcg/L of aluminum.

Laboratory Tests

During the initial treatment of patients with pernicious anemia, serum potassium must be observed closely the first 48 hours and potassium replaced if necessary.

Hematocrit, reticulocyte count, Vitamin B12, folate and iron levels should be obtained prior to treatment. Hematocrit and reticulocyte counts should be repeated daily from the 5thto 7thdays of therapy and then frequently until the hematocrit is normal. If folate levels are low, folic acid should also be administered. If reticulocytes have not increased after treatment or if reticulocyte counts do not continue at least twice normal as long as the hematocrit is less than 35%, diagnosis or treatment should be reevaluated. Repeat determinations of iron and folic acid may reveal a complicating illness that might inhibit the response of the marrow.

Patients with pernicious anemia have about three times the incidence of carcinoma of the stomach as the general population, so appropriate tests for this condition should be carried out when indicated.

Drug and Laboratory Test Interactions

Persons taking most antibiotics, methotrexate and pyrimethamine invalidate folic acid and Vitamin B12diagnostic blood assays.

Colchicine, para-aminosalicylic acid and heavy alcohol intake for longer than two weeks may produce malabsorption of Vitamin B12.

Carcinogenesis, Mutagenesis

Long-term studies in animals to evaluate carcinogenic potential have not been done. There is no evidence from long-term use in patients with pernicious anemia that cyanocobalamin is carcinogenic. Pernicious anemia is associated with an increased incidence of carcinoma of the stomach, but this is believed to be related to the underlying pathology and not to treatment with cyanocobalamin.

Pregnancy

Adequate and well-controlled studies have not been done in pregnant women. However, Vitamin B12is an essential vitamin and requirements are increased during pregnancy. Amounts of Vitamin B12that are recommended by the Food and Nutrition Board, National Academy of Science-National Research Council for pregnant women (4 mcg daily) should be consumed during pregnancy.

Nursing Mothers

Vitamin B12is known to be excreted in human milk. Amounts of Vitamin B12that are recommended by the Food and Nutrition Board, National Academy of Science-National Research Council for lactating women (4 mcg daily) should be consumed during lactation.

Pediatric Use

Intake in children should be in the amount (0.5 to 3 mcg daily) recommended by the Food and Nutrition Board, National Academy of Science-National Research Council.

ADVERSE REACTIONS

Generalized

Anaphylactic shock and death have been reported with administration of parenteral Vitamin B12(see WARNINGS).

Cardiovascular

Pulmonary edema and congestive heart failure early in treatment; peripheral vascular thrombosis.

Hematological

Polycythemia vera.

Gastrointestinal

Mild transient diarrhea.

Dermatological

Itching; transitory exanthema.

Miscellaneous

Feeling of swelling of entire body.

OVERDOSAGE

No overdosage has been reported with this drug.

DOSAGE AND ADMINISTRATION

Avoid using the intravenous route. Use of this product intravenously will result in almost all of the vitamin being lost in the urine.

Pernicious Anemia

Parenteral Vitamin B12is the recommended treatment and will be required for the remainder of the patient's life. The oral form is not dependable. A dose of 100 mcg daily for six or seven days should be administered by intramuscular or deep subcutaneous injection. If there is clinical improvement and if a reticulocyte response is observed, the same amount may be given on alternate days for seven doses, then every three to four days for another two to three weeks. By this time hematologic values should have become normal. This regimen should be followed by 100 mcg monthly for life. Folic acid should be administered concomitantly if needed.

Patients with Normal Intestinal Absorption

Where the oral route is not deemed adequate, initial treatment similar to that for patients with pernicious anemia may be indicated depending on the severity of the deficiency. Chronic treatment should be with an oral B12preparation. If other vitamin deficiencies are present, they should be treated.

Schilling Test

The flushing dose is 1,000 mcg.

Parenteral drug products should be inspected visually for particulate matter and discoloration prior to administration, whenever solution and container permit.

HOW SUPPLIED

1 mL multiple dose vial (NDC 85766-029-01 relabeled from NDC 70069-005-01), packaged 25 vials per tray (NDC 85766-029-25 relabeled from NDC 70069-005-10).

Store at 20° to 25°C (68° to 77°F) [see USP Controlled Room Temperature].

PROTECT FROM LIGHT

Use only if solution is clear and seal intact.

For Product Inquiry call 1-800-417-9175

Distributed by:

Sportpharm LLC
379 Van Ness Ave 1401,
Torrance, CA 90501

Relabeled by:

Enovachem PHARMACEUTICALS

Torrance, CA 90501